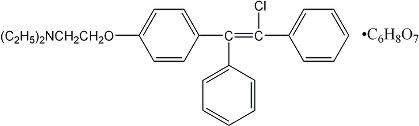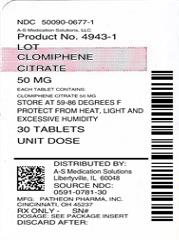 DRUG LABEL: Clomiphene Citrate
NDC: 50090-0677 | Form: TABLET
Manufacturer: A-S Medication Solutions
Category: prescription | Type: HUMAN PRESCRIPTION DRUG LABEL
Date: 20180518

ACTIVE INGREDIENTS: CLOMIPHENE CITRATE 50 mg/1 1
INACTIVE INGREDIENTS: STARCH, CORN; LACTOSE, UNSPECIFIED FORM; MAGNESIUM STEARATE; SUCROSE

70025264
Clomiphene Citrate Tablets USP
Revised: November 2012
Rx only

DESCRIPTION

Clomiphene citrate tablets USP is an orally administered, nonsteroidal, ovulatory stimulant designated chemically as 2-[p-(2-chloro-1,2-diphenylvinyl)phenoxy] triethylamine citrate (1:1). It has the molecular formula of C26H28ClNO • C6H8O7 and a molecular weight of 598.09. It is represented structurally as:

Clomiphene citrate is a white to pale yellow, essentially odorless, crystalline powder. It is freely soluble in methanol; soluble in ethanol; slightly soluble in acetone, water, and chloroform; and insoluble in ether.

Clomiphene citrate tablets USP is a mixture of two geometric isomers [cis (zuclomiphene) and trans (enclomiphene)] containing between 30% and 50% of the cis-isomer.

Each white scored tablet contains 50 mg clomiphene citrate USP, which is the molar equivalent of 34 mg of the clomiphene base. The tablet also contains the following inactive ingredients: corn starch, lactose, magnesium stearate, pregelatinized corn starch, and sucrose.

CLINICAL PHARMACOLOGY

Action

Clomiphene citrate tablets USP is a drug of considerable pharmacologic potency. With careful selection and proper management of the patient, clomiphene citrate tablets USP has been demonstrated to be a useful therapy for the anovulatory patient desiring pregnancy.

Clomiphene citrate is capable of interacting with estrogen-receptor-containing tissues, including the hypothalamus, pituitary, ovary, endometrium, vagina, and cervix. It may compete with estrogen for estrogen-receptor-binding sites and may delay replenishment of intracellular estrogen receptors. Clomiphene citrate initiates a series of endocrine events culminating in a preovulatory gonadotropin surge and subsequent follicular rupture. The first endocrine event in response to a course of clomiphene therapy is an increase in the release of pituitary gonadotropins. This initiates steroidogenesis and folliculogenesis, resulting in growth of the ovarian follicle and an increase in the circulating level of estradiol. Following ovulation, plasma progesterone and estradiol rise and fall as they would in a normal ovulatory cycle.

Available data suggest that both the estrogenic and antiestrogenic properties of clomiphene may participate in the initiation of ovulation. The two clomiphene isomers have been found to have mixed estrogenic and antiestrogenic effects, which may vary from one species to another. Some data suggest that zuclomiphene has greater estrogenic activity than enclomiphene.

Clomiphene citrate has no apparent progestational, androgenic, or antiandrogenic effects and does not appear to interfere with pituitary-adrenal or pituitary-thyroid function.

Although there is no evidence of a "carryover effect" of clomiphene citrate tablets USP, spontaneous ovulatory menses have been noted in some patients after clomiphene citrate tablets USP therapy.

Pharmacokinetics

Based on early studies with ^14C-labeled clomiphene citrate, the drug was shown to be readily absorbed orally in humans and excreted principally in the feces. Cumulative urinary and fecal excretion of the ^14C averaged about 50% of the oral dose and 37% of an intravenous dose after 5 days. Mean urinary excretion was approximately 8% with fecal excretion of about 42%.

Some ^14C label was still present in the feces 6 weeks after administration. Subsequent single-dose studies in normal volunteers showed that zuclomiphene (cis) has a longer half-life than enclomiphene (trans). Detectable levels of zuclomiphene persisted for longer than a month in these subjects. This may be suggestive of stereo-specific enterohepatic recycling or sequestering of the zuclomiphene. Thus, it is possible that some active drug may remain in the body during early pregnancy in women who conceive in the menstrual cycle during clomiphene citrate tablets USP therapy.

CLINICAL STUDIES

During clinical investigations, 7578 patients received clomiphene citrate tablets USP, some of whom had impediments to ovulation other than ovulatory dysfunction (see INDICATIONS AND USAGE). In those clinical trials, successful therapy characterized by pregnancy occurred in approximately 30% of these patients.

There were a total of 2635 pregnancies reported during the clinical trial period. Of those pregnancies, information on outcome was only available for 2369 of the cases. Table 1 summarizes the outcome of these cases.

Of the reported pregnancies, the incidence of multiple pregnancies was 7.98%: 6.9% twin, 0.5% triplet, 0.3% quadruplet, and 0.1% quintuplet. Of the 165 twin pregnancies for which sufficient information was available, the ratio of monozygotic to dizygotic twins was about 1:5. Table 1 reports the survival rate of the live multiple births.

A sextuplet birth was reported after completion of original clinical studies; none of the sextuplets survived (each weighed less than 400 g), although each appeared grossly normal.

Table 1. Outcome of Reported Pregnancies in Clinical Trials (n = 2369)
Outcome | Total Number of Pregnancies | Survival Rate
Pregnancy Wastage
Spontaneous Abortions | 483*
Stillbirths | 24
Live Births
Single Births | 1697 | 98.16%†
Multiple Births | 165 | 83.26%†

* Includes 28 ectopic pregnancies, 4 hydatiform moles, and 1 fetus papyraceous.
† Indicates percentage of surviving infants from these pregnancies.

The overall survival of infants from multiple pregnancies including spontaneous abortions, stillbirths, and neonatal deaths is 73%.
Fetal/Neonatal Anomalies and Mortality. The following fetal abnormalities have been reported subsequent to pregnancies following ovulation induction therapy with clomiphene citrate tablets USP during clinical trials. Each of the following fetal abnormalities were reported at a rate of <1% (experiences are listed in order of decreasing frequency): Congenital heart lesions, Down syndrome, club foot, congenital gut lesions, hypospadias, microcephaly, harelip and cleft palate, congenital hip, hemangioma, undescended testicles, polydactyly, conjoined twins and teratomatous malformation, patent ductus arteriosus, amaurosis, arteriovenous fistula, inguinal hernia, umbilical hernia, syndactyly, pectus excavatum, myopathy, dermoid cyst of scalp, omphalocele, spina bifida occulta, ichthyosis, and persistent lingual frenulum. Neonatal death and fetal death/stillbirth in infants with birth defects have also been reported at a rate of <1%. The overall incidence of reported congenital anomalies from pregnancies associated with maternal clomiphene citrate tablets USP ingestion during clinical studies was within the range of that reported for the general population.

In addition, reports of congenital anomalies have been received during postmarketing surveillance of clomiphene citrate (see ADVERSE REACTIONS).

INDICATIONS AND USAGE

Clomiphene citrate tablets USP is indicated for the treatment of ovulatory dysfunction in women desiring pregnancy. Impediments to achieving pregnancy must be excluded or adequately treated before beginning clomiphene citrate tablets USP therapy. Those patients most likely to achieve success with clomiphene therapy include patients with polycystic ovary syndrome (see WARNINGS: Ovarian Hyperstimulation Syndrome), amenorrhea-galactorrhea syndrome, psychogenic amenorrhea, post-oral-contraceptive amenorrhea, and certain cases of secondary amenorrhea of undetermined etiology.

Properly timed coitus in relationship to ovulation is important. A basal body temperature graph or other appropriate tests may help the patient and her physician determine if ovulation occurred. Once ovulation has been established, each course of clomiphene citrate tablets USP should be started on or about the 5th day of the cycle. Long-term cyclic therapy is not recommended beyond a total of about six cycles (including three ovulatory cycles). (See DOSAGE AND ADMINISTRATION and PRECAUTIONS.)

Clomiphene citrate tablets USP is indicated only in patients with demonstrated ovulatory dysfunction who meet the conditions described below:

1. Patients who are not pregnant.
2. Patients without ovarian cysts. Clomiphene citrate tablets USP should not be used in patients with ovarian enlargement except those with polycystic ovary syndrome. Pelvic examination is necessary prior to the first and each subsequent course of clomiphene citrate tablets USP treatment.
3. Patients without abnormal vaginal bleeding. If abnormal vaginal bleeding is present, the patient should be carefully evaluated to ensure that neoplastic lesions are not present.
4. Patients with normal liver function.

In addition, patients selected for clomiphene citrate tablets USP therapy should be evaluated in regard to the following:

1. Estrogen Levels. Patients should have adequate levels of endogenous estrogen (as estimated from vaginal smears, endometrial biopsy, assay of urinary estrogen, or from bleeding in response to progesterone). Reduced estrogen levels, while less favorable, do not preclude successful therapy.
2. Primary Pituitary or Ovarian Failure. Clomiphene citrate tablets USP therapy cannot be expected to substitute for specific treatment of other causes of ovulatory failure.
3. Endometriosis and Endometrial Carcinoma. The incidence of endometriosis and endometrial carcinoma increases with age as does the incidence of ovulatory disorders. Endometrial biopsy should always be performed prior to clomiphene citrate tablets USP therapy in this population.
4. Other Impediments to Pregnancy. Impediments to pregnancy can include thyroid disorders, adrenal disorders, hyperprolactinemia, and male factor infertility.
5. Uterine Fibroids. Caution should be exercised when using clomiphene citrate tablets USP in patients with uterine fibroids due to the potential for further enlargement of the fibroids.

There are no adequate or well-controlled studies that demonstrate the effectiveness of clomiphene citrate tablets USP in the treatment of male infertility. In addition, testicular tumors and gynecomastia have been reported in males using clomiphene. The cause and effect relationship between reports of testicular tumors and the administration of clomiphene citrate tablets USP is not known.

Although the medical literature suggests various methods, there is no universally accepted standard regimen for combined therapy (ie, clomiphene citrate tablets USP in conjunction with other ovulation-inducing drugs). Similarly, there is no standard clomiphene citrate tablets USP regimen for ovulation induction in in vitro fertilization programs to produce ova for fertilization and reintroduction. Therefore, clomiphene citrate tablets USP is not recommended for these uses.

CONTRAINDICATIONS

Hypersensitivity

Clomiphene citrate tablets USP is contraindicated in patients with a known hypersensitivity or allergy to clomiphene citrate or to any of its ingredients.

Pregnancy

Clomiphene citrate tablets USP use in pregnant women is contraindicated, as clomiphene citrate does not offer benefit in this population.

Available human data do not suggest an increased risk for congenital anomalies above the background population risk when used as indicated. However, animal reproductive toxicology studies showed increased embryo-fetal loss and structural malformations in offspring. If this drug is used during pregnancy, or if the patient becomes pregnant while taking this drug, the patient should be apprised of the potential risks to the fetus. (See PRECAUTIONS: Pregnancy.)

Liver Disease. Clomiphene citrate tablets USP therapy is contraindicated in patients with liver disease or a history of liver dysfunction (see also INDICATIONS AND USAGE and ADVERSE REACTIONS).

Abnormal Uterine Bleeding. Clomiphene citrate tablets USP is contraindicated in patients with abnormal uterine bleeding of undetermined origin (see INDICATIONS AND USAGE).

Ovarian Cysts. Clomiphene citrate tablets USP is contraindicated in patients with ovarian cysts or enlargement not due to polycystic ovarian syndrome (see INDICATIONS AND USAGE and WARNINGS).

Other. Clomiphene citrate tablets USP is contraindicated in patients with uncontrolled thyroid or adrenal dysfunction or in the presence of an organic intracranial lesion such as pituitary tumor (see INDICATIONS AND USAGE).

WARNINGS

Visual Symptoms

Patients should be advised that blurring or other visual symptoms such as spots or flashes (scintillating scotomata) may occasionally occur during therapy with clomiphene citrate tablets USP. These visual symptoms increase in incidence with increasing total dose or therapy duration. These visual disturbances are usually reversible; however, cases of prolonged visual disturbance have been reported with some occurring after clomiphene citrate tablets USP discontinuation. The visual disturbances may be irreversible, especially with increased dosage or duration of therapy. Patients should be warned that these visual symptoms may render such activities as driving a car or operating machinery more hazardous than usual, particularly under conditions of variable lighting.

These visual symptoms appear to be due to intensification and prolongation of afterimages. Symptoms often first appear or are accentuated with exposure to a brightly lit environment. While measured visual acuity usually has not been affected, a study patient taking 200 mg clomiphene citrate tablets USP daily developed visual blurring on the 7th day of treatment, which progressed to severe diminution of visual acuity by the 10th day. No other abnormality was found, and the visual acuity returned to normal on the 3rd day after treatment was stopped.

Ophthalmologically definable scotomata and retinal cell function (electroretinographic) changes have also been reported. A patient treated during clinical studies developed phosphenes and scotomata during prolonged clomiphene citrate tablets USP administration, which disappeared by the 32nd day after stopping therapy.

Postmarketing surveillance of adverse events has also revealed other visual signs and symptoms during clomiphene citrate tablets USP therapy (see ADVERSE REACTIONS).

While the etiology of these visual symptoms is not yet understood, patients with any visual symptoms should discontinue treatment and have a complete ophthalmological evaluation carried out promptly.

Ovarian Hyperstimulation Syndrome

The ovarian hyperstimulation syndrome (OHSS) has been reported to occur in patients receiving clomiphene citrate therapy for ovulation induction. OHSS may progress rapidly (within 24 hours to several days) and become a serious medical disorder. In some cases, OHSS occurred following cyclic use of clomiphene citrate therapy or when clomiphene citrate was used in combination with gonadotropins. Transient liver function test abnormalities suggestive of hepatic dysfunction, which may be accompanied by morphologic changes on liver biopsy, have been reported in association with OHSS.

OHSS is a medical event distinct from uncomplicated ovarian enlargement. The clinical signs of this syndrome in severe cases can include gross ovarian enlargement, gastrointestinal symptoms, ascites, dyspnea, oliguria, and pleural effusion. In addition, the following symptoms have been reported in association with this syndrome: pericardial effusion, anasarca, hydrothorax, acute abdomen, hypotension, renal failure, pulmonary edema, intraperitoneal and ovarian hemorrhage, deep venous thrombosis, torsion of the ovary, and acute respiratory distress. The early warning signs of OHSS are abdominal pain and distention, nausea, vomiting, diarrhea, and weight gain. Elevated urinary steroid levels, varying degrees of electrolyte imbalance, hypovolemia, hemoconcentration, and hypoproteinemia may occur. Death due to hypovolemic shock, hemoconcentration, or thromboembolism has occurred. Due to fragility of enlarged ovaries in severe cases, abdominal and pelvic examination should be performed very cautiously. If conception results, rapid progression to the severe form of the syndrome may occur.

To minimize the hazard associated with occasional abnormal ovarian enlargement associated with clomiphene citrate tablets USP therapy, the lowest dose consistent with expected clinical results should be used. Maximal enlargement of the ovary, whether physiologic or abnormal, may not occur until several days after discontinuation of the recommended dose of clomiphene citrate tablets USP. Some patients with polycystic ovary syndrome who are unusually sensitive to gonadotropin may have an exaggerated response to usual doses of clomiphene citrate tablets USP. Therefore, patients with polycystic ovary syndrome should be started on the lowest recommended dose and shortest treatment duration for the first course of therapy (see DOSAGE AND ADMINISTRATION).

If enlargement of the ovary occurs, additional clomiphene citrate tablets USP therapy should not be given until the ovaries have returned to pretreatment size, and the dosage or duration of the next course should be reduced. Ovarian enlargement and cyst formation associated with clomiphene citrate tablets USP therapy usually regress spontaneously within a few days or weeks after discontinuing treatment. The potential benefit of subsequent clomiphene citrate tablets USP therapy in these cases should exceed the risk. Unless surgical indication for laparotomy exists, such cystic enlargement should always be managed conservatively.

A causal relationship between ovarian hyperstimulation and ovarian cancer has not been determined. However, because a correlation between ovarian cancer and nulliparity, infertility, and age has been suggested, if ovarian cysts do not regress spontaneously, a thorough evaluation should be performed to rule out the presence of ovarian neoplasia.

PRECAUTIONS

General

Careful attention should be given to the selection of candidates for clomiphene citrate tablets USP therapy. Pelvic examination is necessary prior to clomiphene citrate tablets USP treatment and before each subsequent course (see CONTRAINDICATIONS and WARNINGS).

Information for Patients

The purpose and risks of clomiphene citrate tablets USP therapy should be presented to the patient before starting treatment. It should be emphasized that the goal of clomiphene citrate tablets USP therapy is ovulation for subsequent pregnancy. The physician should counsel the patient with special regard to the following potential risks:

Visual Symptoms: Advise that blurring or other visual symptoms occasionally may occur during or shortly after clomiphene citrate tablets USP therapy. It should be made clear to the patient that, in some instances, visual disturbances may be prolonged, and possibly irreversible, especially with increased dosage or duration of therapy. Warn that visual symptoms may render such activities as driving a car or operating machinery more hazardous than usual, particularly under conditions of variable lighting (see WARNINGS).

The patient should be instructed to inform the physician whenever any unusual visual symptoms occur. If the patient has any visual symptoms, treatment should be discontinued and complete ophthalmologic evaluation performed.

Abdominal/Pelvic Pain or Distention: Ovarian enlargement may occur during or shortly after therapy with clomiphene citrate tablets USP. To minimize the risks associated with ovarian enlargement, the patient should be instructed to inform the physician of any abdominal or pelvic pain, weight gain, discomfort, or distention after taking clomiphene citrate tablets USP (see WARNINGS).

Metabolism Disorders: Cases of hypertriglyceridemia have been reported. Preexisting or family history of hyperlipidemia and use of higher than recommended dose and/or longer duration of treatment with clomiphene citrate are associated with a risk of hypertriglyceridemia. Periodic monitoring of plasma triglycerides is recommended in patients with preexisting or family history of hyperlipidemia (see ADVERSE REACTIONS). Pre-treatment screening of triglyceride levels is recommended in patients initiating Clomid therapy.

Gastrointestinal Disorders: Cases of pancreatitis have been reported.

Multiple Pregnancy: Inform the patient that there is an increased chance of multiple pregnancy, including bilateral tubal pregnancy and coexisting tubal and intrauterine pregnancy, when conception occurs in relation to clomiphene citrate tablets USP therapy. The potential complications and hazards of multiple pregnancy should be explained.

Spontaneous Abortion and Congenital Anomalies: Inform the patient that the available data suggest no increase in the rates of spontaneous abortion (miscarriage) or congenital anomalies with maternal clomiphene citrate tablets USP use compared to rates in the general population.

During clinical investigation, the experience from patients with known pregnancy outcome (Table 1) shows a spontaneous abortion rate of 20.4% and stillbirth rate of 1.0%. (See CLINICAL STUDIES). Among the birth anomalies spontaneously reported as individual cases since commercial availability of clomiphene citrate tablets USP, the proportion of neural tube defects has been high among pregnancies associated with ovulation induced by clomiphene citrate tablets USP, but this has not been supported by data from population-based studies.

Drug Interactions

Drug interactions with clomiphene citrate tablets USP have not been documented.

Carcinogenesis, Mutagenesis, Impairment of Fertility

Long-term toxicity studies in animals have not been performed to evaluate the carcinogenic or mutagenic potential of clomiphene citrate.

Oral administration of clomiphene citrate tablets USP to male rats at doses of 0.3 or 1 mg/kg/day caused decreased fertility, while higher doses caused temporary infertility. Oral doses of 0.1 mg/kg/day in female rats temporarily interrupted the normal cyclic vaginal smear pattern and prevented conception. Doses of 0.3 mg/kg/day slightly reduced the number of ovulated ova and corpora lutea, while 3 mg/kg/day inhibited ovulation.

Pregnancy

Fetal Risk Summary

Clomiphene citrate use in pregnant women is contraindicated, as clomiphene citrate tablets USP treatment does not offer benefit in this population.

Available human data do not suggest an increased risk for congenital anomalies above the background population risk. However, animal reproductive toxicology studies showed increased embryo-fetal loss and structural malformations in offspring. If this drug is used during pregnancy, or if the patient becomes pregnant while taking this drug, the patient should be apprised of the potential risks to the fetus.

Clinical Considerations

To avoid inadvertent clomiphene citrate tablets USP administration during early pregnancy, appropriate tests should be utilized during each treatment cycle to determine whether ovulation and/or pregnancy occurs. Patients should be evaluated carefully to exclude ovarian enlargement or ovarian cyst formation between each treatment cycle. The next course of clomiphene citrate USP therapy should be delayed until these conditions have been excluded.

Human data

The available human data from epidemiologic studies do not show any apparent cause and effect relationship between clomiphene citrate tablets USP periconceptual exposure and an increased risk of overall birth defects, or any specific anomaly. However, due to the small number of cases of congenital anomalies occurring in clomiphene citrate tablets USP treated women, these epidemiologic studies were only able to rule out large differences in risk. The studies did not consider factors associated with female subfertility and were unable to adjust for other important confounders.

In addition, available data do not support an increased rate of spontaneous abortion among subfertile women treated with clomiphene citrate for ovulation induction.

Animal data

Oral administration of clomiphene citrate to pregnant rats during organogenesis at doses of 1 to 2 mg/kg/day resulted in hydramnion and weak, edematous fetuses with wavy ribs and other temporary bone changes. Doses of 8 mg/kg/day or more also caused increased resorptions and dead fetuses, dystocia, and delayed parturition, and 40 mg/kg/day resulted in increased maternal mortality. Single doses of 50 mg/kg caused fetal cataracts, while 200 mg/kg caused cleft palate. Following injection of clomiphene citrate 2 mg/kg to mice and rats during pregnancy, the offspring exhibited metaplastic changes of the reproductive tract. Newborn mice and rats injected during the first few days of life also developed metaplastic changes in uterine and vaginal mucosa, as well as premature vaginal opening and anovulatory ovaries. These findings are similar to the abnormal reproductive behavior and sterility described with other estrogens and antiestrogens.

In rabbits, some temporary bone alterations were seen in fetuses from dams given oral doses of 20 or 40 mg/kg/day during pregnancy, but not following 8 mg/kg/day. No permanent malformations were observed in those studies. Also, rhesus monkeys given oral doses of 1.5 to 4.5 mg/kg/day for various periods during pregnancy did not have any abnormal offspring.

Nursing Mothers

It is not known whether clomiphene citrate tablets USP is excreted in human milk. Because many drugs are excreted in human milk, caution should be exercised if clomiphene citrate tablets USP is administered to a nursing woman. In some patients, clomiphene citrate tablets USP may reduce lactation.

Ovarian Cancer

Prolonged use of clomiphene citrate tablets USP may increase the risk of a borderline or invasive ovarian tumor (see ADVERSE REACTIONS).

ADVERSE REACTIONS

Clinical Trial Adverse Events. Clomiphene citrate tablets USP, at recommended dosages, is generally well tolerated. Adverse reactions usually have been mild and transient and most have disappeared promptly after treatment has been discontinued. Adverse experiences reported in patients treated with clomiphene citrate during clinical studies are shown in Table 2.

Table 2. Incidence of Adverse Events in Clinical Studies (Events Greater than 1%) (n = 8029*)
Adverse Event | %
Ovarian Enlargement | 13.6
Vasomotor Flushes | 10.4
Abdominal-Pelvic Discomfort/Distention/Bloating | 5.5
Nausea and Vomiting | 2.2
Breast Discomfort | 2.1
Visual Symptoms | 1.5
Blurred vision, lights, floaters, waves, unspecified visual complaints, photophobia, diplopia, scotomata, phosphenes
Headache | 1.3
Abnormal Uterine Bleeding | 1.3
Intermenstrual spotting, menorrhagia

* Includes 498 patients whose reports may have been duplicated in the event totals and could not be distinguished as such. Also, excludes 47 patients who did not report symptom data.
The following adverse events have been reported in fewer than 1% of patients in clinical trials: Acute abdomen, appetite increase, constipation, dermatitis or rash, depression, diarrhea, dizziness, fatigue, hair loss/dry hair, increased urinary frequency/volume, insomnia, light-headedness, nervous tension, vaginal dryness, vertigo, weight gain/loss.

Patients on prolonged clomiphene citrate tablets USP therapy may show elevated serum levels of desmosterol. This is most likely due to a direct interference with cholesterol synthesis. However, the serum sterols in patients receiving the recommended dose of clomiphene citrate tablets USP are not significantly altered. Ovarian cancer has been infrequently reported in patients who have received fertility drugs. Infertility is a primary risk factor for ovarian cancer; however, epidemiology data suggest that prolonged use of clomiphene citrate tablets USP may increase the risk of a borderline or invasive ovarian tumor.

Postmarketing Adverse Events

The following adverse reactions have been identified during post approval use of clomiphene citrate. Because these reactions are reported voluntarily from a population of uncertain size, it is not always possible to reliably estimate their frequency or establish a causal relationship to drug exposure.

Body as a Whole: Fever, tinnitus, weakness

Cardiovascular: Arrhythmia, chest pain, edema, hypertension, palpitation, phlebitis, pulmonary embolism, shortness of breath, tachycardia, thrombophlebitis

Central Nervous System: Dizziness, migraine headache, paresthesia, seizure, stroke, syncope, transient parasthesia

Dermatologic: Acne, allergic reaction, erythema, erythema multiforme, erythema nodosum, hypertrichosis, pruritus, urticaria

Fetal/Neonatal Anomalies:

• Abnormal bone development: skeletal malformations of the skull, face, nasal passages, jaw, hand, limb (ectromelia including amelia, hemimelia, and phocomelia), foot (clubfoot), spine, and joints

• Cardiac abnormalities: septal heart defects, muscular ventricular septal defect, patent ductus arteriosus, tetralogy of Fallot, and coarctation of the aorta

• Chromosomal disorders: Downs syndrome

• Ear abnormalities and deafness

• Gastrointestinal tract abnormalities: cleft lip and palate, imperforate anus, tracheoesophageal fistula, diaphragmatic hernia, omphalocele

• Genitalia abnormalities: hypospadias, cloacal exstrophy

• Lung tissue malformations

• Malformations of the eye and lens (cataract)

• Neoplasms: neuroectodermal tumor, thyroid tumor, hepatoblastoma, lymphocytic leukemia

• Nervous system abnormalities: neural tube defects (anencephaly, meningomyelocele), microcephaly, and hydrocephalus

• Renal abnormalities: renal agenesis and renal dysgenesis

• Others: dwarfism, mental retardation

Gastrointestinal: Pancreatitis

Genitourinary: Endometriosis, ovarian cyst (ovarian enlargement or cysts could, as such, be complicated by adnexal torsion), ovarian hemorrhage, tubal pregnancy, uterine hemorrhage, reduced endometrial thickness

Hepatic: Transaminases increased, hepatitis

Metabolism Disorders: Hypertriglyceridemia, in some cases with pancreatitis

Musculoskeletal: Arthralgia, back pain, myalgia

Neoplasms: Liver (hepatic hemangiosarcoma, liver cell adenoma, hepatocellular carcinoma); breast (fibrocystic disease, breast carcinoma); endometrium (endometrial carcinoma); nervous system (astrocytoma, pituitary tumor, prolactinoma, neurofibromatosis, glioblastoma multiforme, brain abcess); ovary (luteoma of pregnancy, dermoid cyst of the ovary, ovarian carcinoma); trophoblastic (hydatiform mole, choriocarcinoma); miscellaneous (melanoma, myeloma, perianal cysts, renal cell carcinoma, Hodgkin's lymphoma, tongue carcinoma, bladder carcinoma)

Psychiatric: Anxiety, depression, insomnia, irritability, mood disturbances (including mood altered, mood swings and irritability) nervousness, psychosis

Visual Disorders: Abnormal accommodation, cataract, eye pain, macular edema, optic neuritis, photopsia, posterior vitreous detachment, retinal hemorrhage, retinal thrombosis, retinal vascular spasm, temporary or prolonged loss of vision, possibly irreversible

Other: Leukocytosis, thyroid disorder

DRUG ABUSE AND DEPENDENCE

Tolerance, abuse, or dependence with clomiphene citrate tablets USP has not been reported.

OVERDOSAGE

Signs and Symptoms

Toxic effects accompanying acute overdosage of clomiphene citrate tablets USP have not been reported. Signs and symptoms of overdosage as a result of the use of more than the recommended dose during clomiphene citrate tablets USP therapy include nausea, vomiting, vasomotor flushes, visual blurring, spots or flashes, scotomata, ovarian enlargement with pelvic or abdominal pain. (See CONTRAINDICATIONS: Ovarian Cyst.)

Oral LD50. The acute oral LD50 of clomiphene citrate tablets USP is 1700 mg/kg in mice and 5750 mg/kg in rats. The toxic dose in humans is not known.

Dialysis. It is not known if clomiphene citrate tablets USP is dialyzable.

Treatment

In the event of overdose, appropriate supportive measures should be employed in addition to gastrointestinal decontamination.

DOSAGE AND ADMINISTRATION

General Considerations

The workup and treatment of candidates for clomiphene citrate tablets USP therapy should be supervised by physicians experienced in management of gynecologic or endocrine disorders. Patients should be chosen for therapy with clomiphene citrate tablets USP only after careful diagnostic evaluation (see INDICATIONS AND USAGE). The plan of therapy should be outlined in advance. Impediments to achieving the goal of therapy must be excluded or adequately treated before beginning clomiphene citrate tablets USP. The therapeutic objective should be balanced with potential risks and discussed with the patient and others involved in the achievement of a pregnancy.

Ovulation most often occurs from 5 to 10 days after a course of clomiphene citrate tablets USP. Coitus should be timed to coincide with the expected time of ovulation. Appropriate tests to determine ovulation may be useful during this time.

Recommended Dosage

Treatment of the selected patient should begin with a low dose, 50 mg daily (1 tablet) for 5 days. The dose should be increased only in those patients who do not ovulate in response to cyclic 50 mg clomiphene citrate tablets USP. A low dosage or duration of treatment course is particularly recommended if unusual sensitivity to pituitary gonadotropin is suspected, such as in patients with polycystic ovary syndrome (see WARNINGS; Ovarian Hyperstimulation Syndrome).

The patient should be evaluated carefully to exclude pregnancy, ovarian enlargement, or ovarian cyst formation between each treatment cycle.

If progestin-induced bleeding is planned, or if spontaneous uterine bleeding occurs prior to therapy, the regimen of 50 mg daily for 5 days should be started on or about the 5th day of the cycle. Therapy may be started at any time in the patient who has had no recent uterine bleeding. When ovulation occurs at this dosage, there is no advantage to increasing the dose in subsequent cycles of treatment.

If ovulation does not appear to occur after the first course of therapy, a second course of 100 mg daily (two 50 mg tablets given as a single daily dose) for 5 days should be given. This course may be started as early as 30 days after the previous one after precautions are taken to exclude the presence of pregnancy. Increasing the dosage or duration of therapy beyond 100 mg/day for 5 days is not recommended.

The majority of patients who are going to ovulate will do so after the first course of therapy. If ovulation does not occur after three courses of therapy, further treatment with clomiphene citrate tablets USP is not recommended and the patient should be reevaluated. If three ovulatory responses occur, but pregnancy has not been achieved, further treatment is not recommended. If menses does not occur after an ovulatory response, the patient should be reevaluated. Long-term cyclic therapy is not recommended beyond a total of about 6 cycles (see PRECAUTIONS).

HOW SUPPLIED

Product: 50090-0677

NDC: 50090-0677-1 30 TABLET in a CARTON